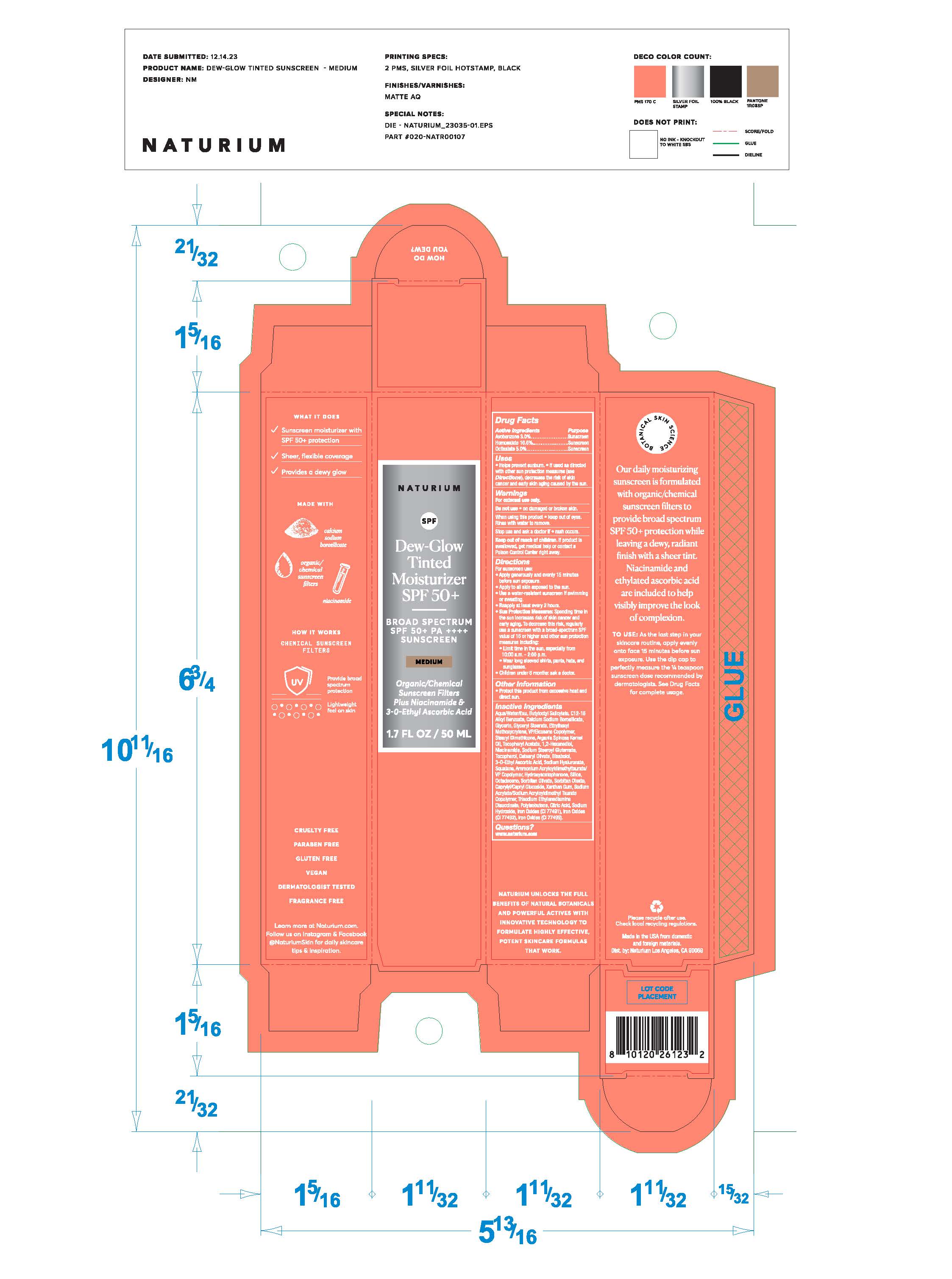 DRUG LABEL: Naturium Dew Glow Tinted Moisturizer SPF50-medium
NDC: 76354-132 | Form: LOTION
Manufacturer: e.l.f. Cosmetics, Inc.
Category: otc | Type: HUMAN OTC DRUG LABEL
Date: 20251114

ACTIVE INGREDIENTS: HOMOSALATE 10 g/50 mL; AVOBENZONE 3 g/50 mL; OCTISALATE 5 g/50 mL
INACTIVE INGREDIENTS: NIACINAMIDE; SORBITAN MONOOLEATE; TOCOPHEROL; 3-O-ETHYL ASCORBIC ACID; OCTADECENE; XANTHAN GUM; POLYISOBUTYLENE (400000 MW); ALKYL (C12-15) BENZOATE; GLYCERYL MONOSTEARATE; BUTYLOCTYL SALICYLATE; ANHYDROUS CITRIC ACID; SODIUM HYDROXIDE; HYDROXYACETOPHENONE; CETEARYL OLIVATE; BROWN IRON OXIDE; .ALPHA.-TOCOPHEROL ACETATE; HYALURONIC ACID; SODIUM ACRYLATE/SODIUM ACRYLOYLDIMETHYLTAURATE COPOLYMER (4000000 MW); WATER; GLYCERIN; VINYLPYRROLIDONE/EICOSENE COPOLYMER; .ALPHA.-BISABOLOL, (+)-; BOROSILICATE GLASS; ARGAN OIL; SODIUM STEAROYL GLUTAMATE; AMMONIUM ACRYLOYLDIMETHYLTAURATE/VP COPOLYMER; SILICON DIOXIDE; 1,2-HEXANEDIOL; SQUALANE; SORBITAN OLIVATE; CAPRYLYL/CAPRYL OLIGOGLUCOSIDE; TRISODIUM ETHYLENEDIAMINE DISUCCINATE

Naturium Dew-Glow Tinted Moisturizer SPF50-medium

ACTIVE INGREDIENT

Avobenzone 3.0%

Homosalate 10.0%

Octisalate 5.0%

PURPOSE

Sunscreen

Uses

Helps prevent sunburn.

If used as directed with other sun protection measures (see Directions), decreases the risk of skin cancer and early signs of aging caused by the sun.

WARNINGS

For external use only.

DO NOT USE

on damaged or broken skin.

WHEN USING

keep out of eyes. Rinse with water to remove.

KEEP OUT OF REACH OF CHILDREN

if product is swallowed, get medical help or contact a Poison Control Center right away.

Directions

For sunscreen use:

Apply generously and evenly 15 minutes before sun exposure.

Apply to all skin exposed to the sun.

Use a water-resistant sunscreen if swimming or sweating.

Reapply at least every 2 hours.

Sun Protection Measures: Spending time in the sun increases risk of skin cancer and early aging. To decrease this risk, regularly use a sunscreen with a Broad-Spectrum SPF value of 15 or higher and other sun protection measures including:

Limit time in the sun, especially from 10:00 a.m. - 2:00 p.m.

Wear long sleeved shirts, pants, hats, and sunglasses.

Children under 6 months of age: Ask a doctor.

Other Information

Protect this product from excessive heat and direct sun.

INACTIVE INGREDIENT

Aqua/Water/Eau, Butyloctyl Salicylate, C12-15 Alkyl Benzoate, Calcium Sodium Borosilicate, Glycerin, Glyceryl Stearate, Ethylhexyl Methoxycrylene, VP/Eicosene Copolymer, Stearyl Dimethicone, Argania Spinosa Kernel Oil, Tocopheryl Acetate, 1,2-Hexandiol, Niacinamide, Sodium Stearoyl Glutamate, Tocopherol, Cetearyl Olivate, Bisabolol, 3-O-Ethyl Ascorbic Acid, Sodium Hyaluronate, Squalane, Ammonium Acryloyldimethyltaurate/VP Copolymer, Hydroxyacetophnone, Silica, Octadecene, Sorbitan Olivate, Sorbitan Oleate, Caprylyl/Capryl Glucoside, Xanthan Gum, Sodium Acrylate/Sodium Acryloyldimethyltaurate/VP Copolymer, Hydroxyacetophenone, Silica, Octadecene, Sorbitan Olivate, Sorbitan Oleate, Caprylyl/Capryl Glucoside, Xanthan Gum, Sodium Acrylate/Sodium Acryloyldimethyl Taurate Copolymer, Trisodium Ethylenediamine Disuccinate, Polyisobutene, Citric Acid, Sodium Hydroxide

May Contain: Iron Oxide (CI 77491), Iron Oxide (CI 77492), Iron Oxide (CI 77499)

QUESTIONS

www.naturium.com